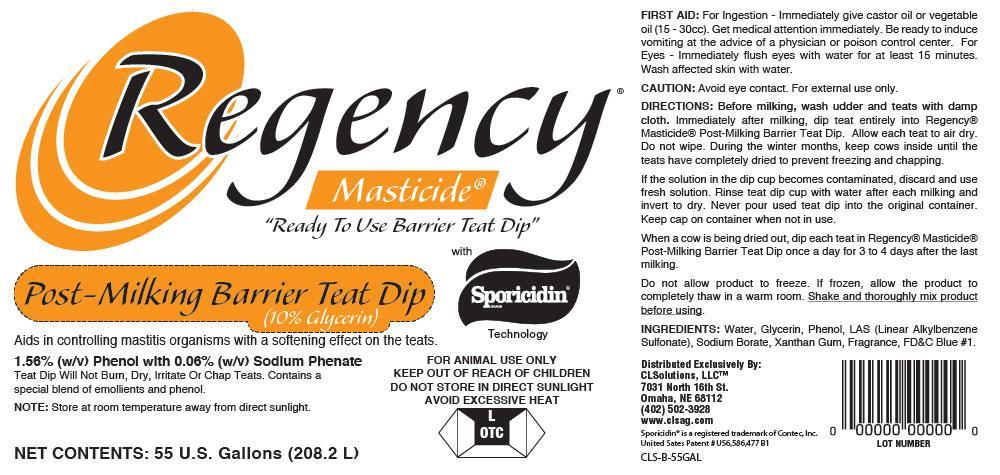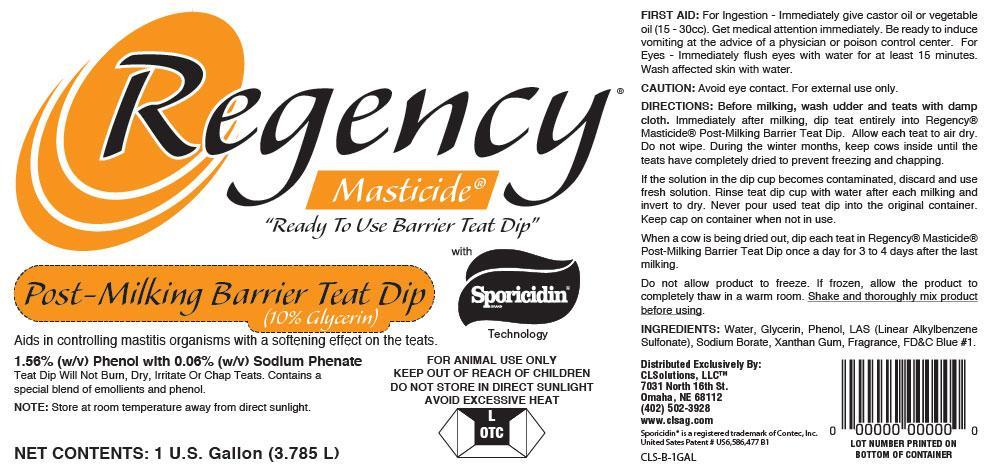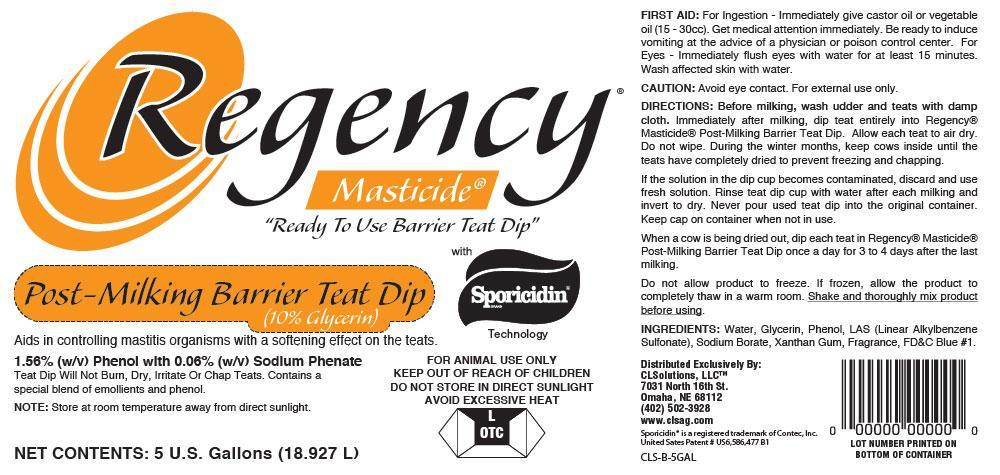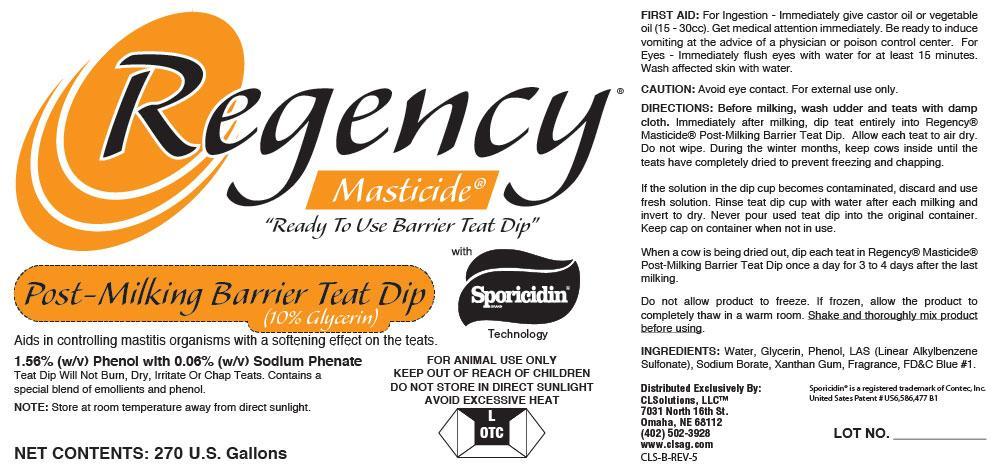 DRUG LABEL: Regnecy Post-Milking Barrier Teat Dip
NDC: 86018-100 | Form: SOLUTION
Manufacturer: CLSolutions, LLC
Category: animal | Type: OTC ANIMAL DRUG LABEL
Date: 20140523

ACTIVE INGREDIENTS: PHENOL 156 g/1 L; PHENOLATE SODIUM 0.06 g/1 L
INACTIVE INGREDIENTS: SODIUM HYDROXIDE; SODIUM BORATE; GLYCERIN; XANTHAN GUM; P-DODECYLBENZENESULFONIC ACID; FD&C BLUE NO. 1; WATER

Regency Post-Milking Barrier Teat Dip

ACTIVE INGREDIENTS:

Active Ingredients |  | Purpose
PHENOL (1.56% w/v) |  | Disinfectant
PHENOLATE SODIUM (0.06% w/v) |  | Disinfectant

PURPOSE:

Active Ingredients |  | Purpose
PHENOL (1.56% w/v) |  | Disinfectant
PHENOLATE SODIUM (0.06% w/v) |  | Disinfectant

Keep Out of Reach of Children.

If swallowed, get medical help or contact Poison Control Center right away.

Uses:

FOR ANIMAL USE ONLY

Aids in controlling mastitis organisms with a softening effect on teats

Directions for Use:

Before milking, wash udder and teats with a damp cloth.

Immediately after milking, dip each teat 1 to 2 inches into Regency Teat Dip.

Allow each teat to air dry. Do not wipe.

During the winter months, keep cows inside until the teats have completely dried to prevent freezing and chapping.

When a cow is being dried out, dip each teat in Regency Post-Milking Barrier Teat Dip once a day for 3 to 4 days after the last milking.

WARNINGS AND PRECAUTIONS

CAUTION:

Avoid eye contact. Do not inhale fumes. For external use only.

FIRST AID:

For Ingestion - Immediately give castor oil or vegetable oil (15-30cc). Get medical attention immediately.

Be ready to induce vomiting at the advice of a physician or poison control center.

For Eyes - Immediately flush eyes with water for at least 15 minutes. Wash affected skin with water.

When using this product:

Do Not Store in Direct Sunlight.

Avoid Excessive Heat.

USER SAFETY WARNINGS:

Do Not Allow Product To Freeze. If frozen, allow the product to completely thaw in a warm room.

Shake and thoroughly mix product before using.

Rinse teat dip cup with water after each milking and invert to dry.

Never pour used teat dip into original container.

Keep cap on container when not in use.

INACTIVE INGREDIENTS:

Water, Glycerin, Linear Alkylbenzene Sulfonate, Sodium Borate, Xanthan Gum, Fragrance, FD&C Blue #1

PACKAGE LABEL

Regency Post-Milking Barrier Teat Dip

Masticide® with Sporicidin™ Technology. "Ready To Use Barrier Teat Dip"

Aids in controlling mastitis organisms with a softening effect on the teats.

1.56% (w/v) Phenol with 0.06% (w/v) Sodium Phenate

Teat Dip Will Not Burn, Dry, Irritate or Chap Teats. Contains a special blend of emolliants and phenol.

NET CONTENTS: 270 U.S. Gallons

PACKAGE LABEL

Regency Post-Milking Barrier Teat Dip

Masticide® with Sporicidin™ Technology. "Ready To Use Barrier Teat Dip"

Aids in controlling mastitis organisms with a softening effect on the teats.

1.56% (w/v) Phenol with 0.06% (w/v) Sodium Phenate

Teat Dip Will Not Burn, Dry, Irritate or Chap Teats. Contains a special blend of emolliants and phenol.

NET CONTENTS: 55 U.S. Gallons (208.2 L)

PACKAGE LABEL

Regency Post-Milking Barrier Teat Dip

Masticide® with Sporicidin™ Technology. "Ready To Use Barrier Teat Dip"

Aids in controlling mastitis organisms with a softening effect on the teats.

1.56% (w/v) Phenol with 0.06% (w/v) Sodium Phenate

Teat Dip Will Not Burn, Dry, Irritate or Chap Teats. Contains a special blend of emolliants and phenol.

NET CONTENTS: 5 Gallons (18.927 L)

PACKAGE LABEL

Regency Post-Milking Barrier Teat Dip

Masticide® with Sporicidin™ Technology. "Ready To Use Barrier Teat Dip"

Aids in controlling mastitis organisms with a softening effect on the teats.

1.56% (w/v) Phenol with 0.06% (w/v) Sodium Phenate

Teat Dip Will Not Burn, Dry, Irritate or Chap Teats. Contains a special blend of emolliants and phenol.

NET CONTENTS: 1 U.S. Gallon (3.785 L)